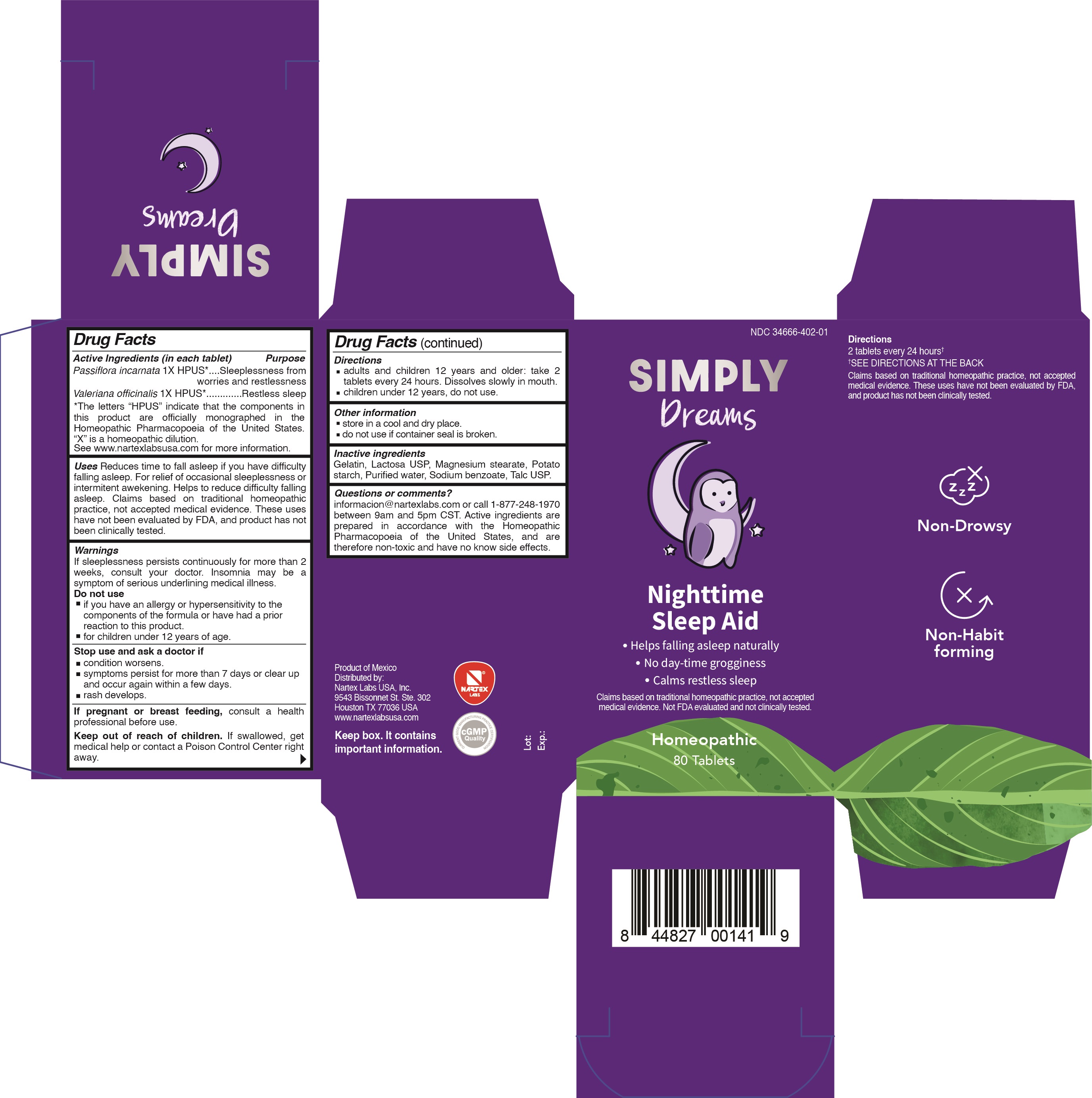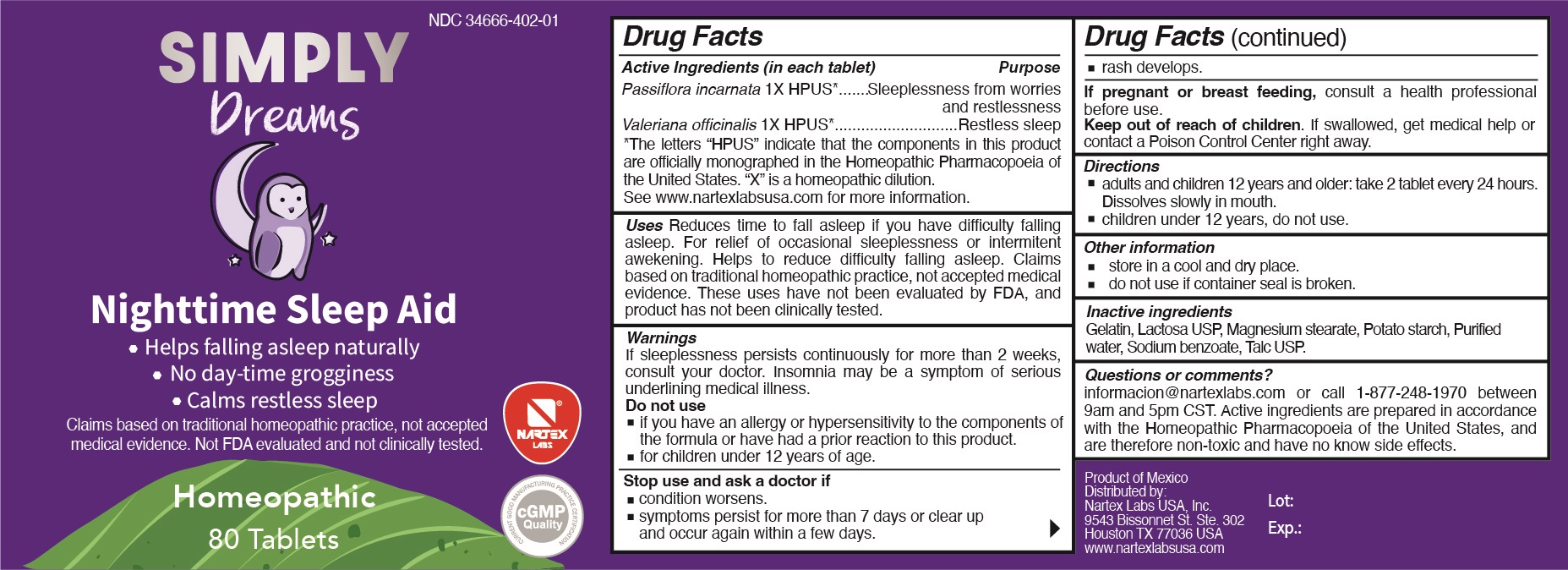 DRUG LABEL: Simply Dreams
NDC: 34666-402 | Form: TABLET
Manufacturer: Nartex Laboratorios Homeopaticos, S.A. De C.V.
Category: homeopathic | Type: HUMAN OTC DRUG LABEL
Date: 20211203

ACTIVE INGREDIENTS: PASSIFLORA INCARNATA FLOWERING TOP 1 [hp_X]/1 1; VALERIAN 1 [hp_X]/1 1
INACTIVE INGREDIENTS: SODIUM BENZOATE; GELATIN; STARCH, POTATO; TALC; MAGNESIUM STEARATE; WATER; LACTOSE, UNSPECIFIED FORM

Simply Dreams

Active ingredients

Passiflora incarnata 1X HPUS*

Valeriana officinalis 1X HPUS*

Purpose

Passiflora incarnata 1X HPUS*...................Sleeplessness from worries and restlessness

Valeriana officinalis 1X HPUS*....................Restless sleep

*The letters "HPUS" indicate that the components in this product are officially monographed in the Homeopathic Pharmacopoeia of the United States. "X" is a homeopathic dilution. See www.nartexlabsusa.com for more information.

Uses

Reduces time to fall asleep if you have difficulty falling asleep. For relief of occasional sleeplessness or intermittent awakening. Helps to reduce difficulty falling asleep. Claims based on traditional homeopathic practice, not accepted medical evidence. These uses have not been evaluated by FDA, and product has not been clinically tested.

Warnings

If sleeplessness persists continuously for more than 2 weeks, consult your doctor. Insomnia may be a symptom of serious underlying medical illness.

Do not use

- if you have an allergy or hypersensitivity to the components of the formula or have had a prior reaction to this product.
- for children under 12 years of age.

Stop use and ask a doctor if

- condition worsens.
- symptoms persist for more than 7 days or clear up and occur again within a few days.
- rash develops.

PREGNANCY OR BREAST FEEDING

If pregnant or breast feeding, consult a health professional before use.

Keep out of reach of children. If swallowed, get medical help or contact a Poison Control Center right away.

Directions

- adults and children 12 years and older: take 2 tablets every 24 hours. Dissolves slowly in mouth.
- children under 12 years, do not use.

Other information

- store in a cool and dry place.
- do not use if container seal is broken.

Inactive ingredients

Gelatin, Lactosa USP, Magnesium stearate, Potato starch, Purified water, Sodium benzoate, Talc USP

Questions or comments?

informacion@nartexlabs.com or call 1-877-248-1970 between 9am and 5pm CST. Active ingredients are prepared in accordance with the Homeopathic Pharmacopoeia of the United States, and are therefore non-toxic and have no known side effects.

PACKAGE LABEL

NDC 34666-402-01

SIMPLY Dreams

Nighttime Sleep Aid

- Helps falling asleep naturally
- No day-time grogginess
- Calms restless sleep

Claims based on traditional homeopathic practice, not accepted medical evidence. Not FDA evaluated and not clinically tested.

Homeopathic

80 Tablets